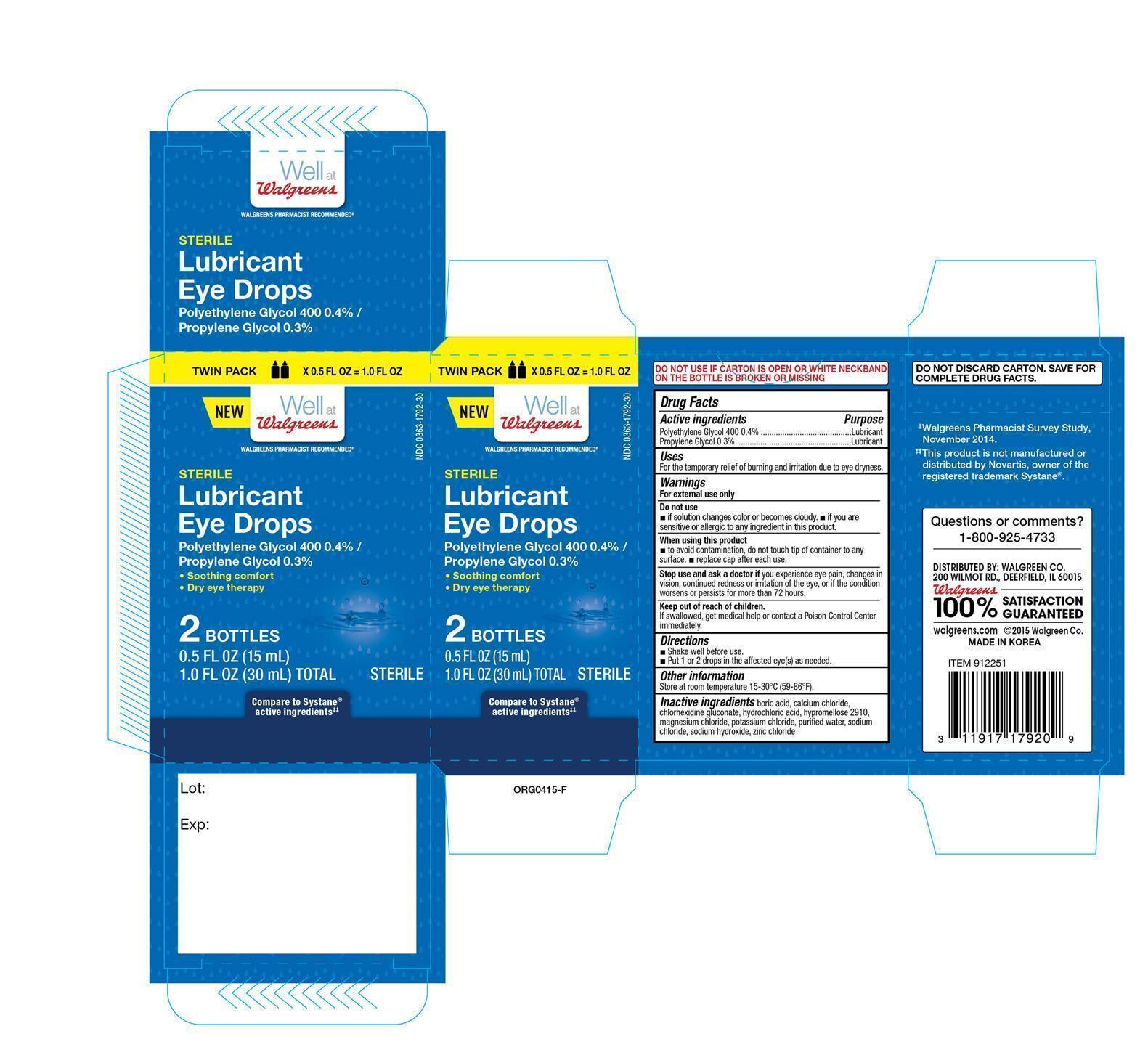 DRUG LABEL: Walgreens Lubricant Eye
NDC: 0363-1792 | Form: SOLUTION/ DROPS
Manufacturer: Walgreen Company
Category: otc | Type: HUMAN OTC DRUG LABEL
Date: 20150923

ACTIVE INGREDIENTS: CARBOXYMETHYLCELLULOSE SODIUM 5 mg/1 mL; GLYCERIN 9 mg/1 mL
INACTIVE INGREDIENTS: BENZALKONIUM CHLORIDE; BORIC ACID; ERYTHRITOL; LEVOCARNITINE; MAGNESIUM CHLORIDE; POTASSIUM CHLORIDE; WATER; SODIUM BORATE

Active ingredients Purpose

Carboxymethylcellulose sodium 0.5%................................. Eye Lubricant

Glycerin 0.9%.................................................................. Eye Lubricant

Uses

- For the temporary relief of burning and irritation due to dryness of the eye or exposure to wind or sun.
- May be used as a protectant against further irritation

Warnings

- For external use only
- To avoid contamination, do not touch tip of container to any surface. Replace cap after using.
- If solution changes color or becomes cloudy, do not use.

Stop use and ask a doctor if you experience eye pain, changes in vision, continued redness or irritation of the eye, or if the condition worsens or persists for more than 72 hours.

Keep out of reach of children.

If swallowed, get medical help or contact a Poison Control Center immediately.

Directions

- Instill 1 or 2 drops in the affected eye(s) as needed.

Other information

- Use before expiration date marked on container.
- Store at 59-86°F (15-30°C)
- RETAIN THIS CARTON FOR FUTURE REFERENCE.

Inactive ingredients

benzalkonium chloride, boric acid, calcium chloride dihydrate, erythritol, levocarnitine, magnesium chloride, potassium chloride, purified water, sodium borate, sodium citrate dihydrate

DOSAGE AND ADMINISTRATION

Distributed by:

Walgreen Co.

200 Wilmot Rd.

Deerfield, IL 60015

Made in Korea